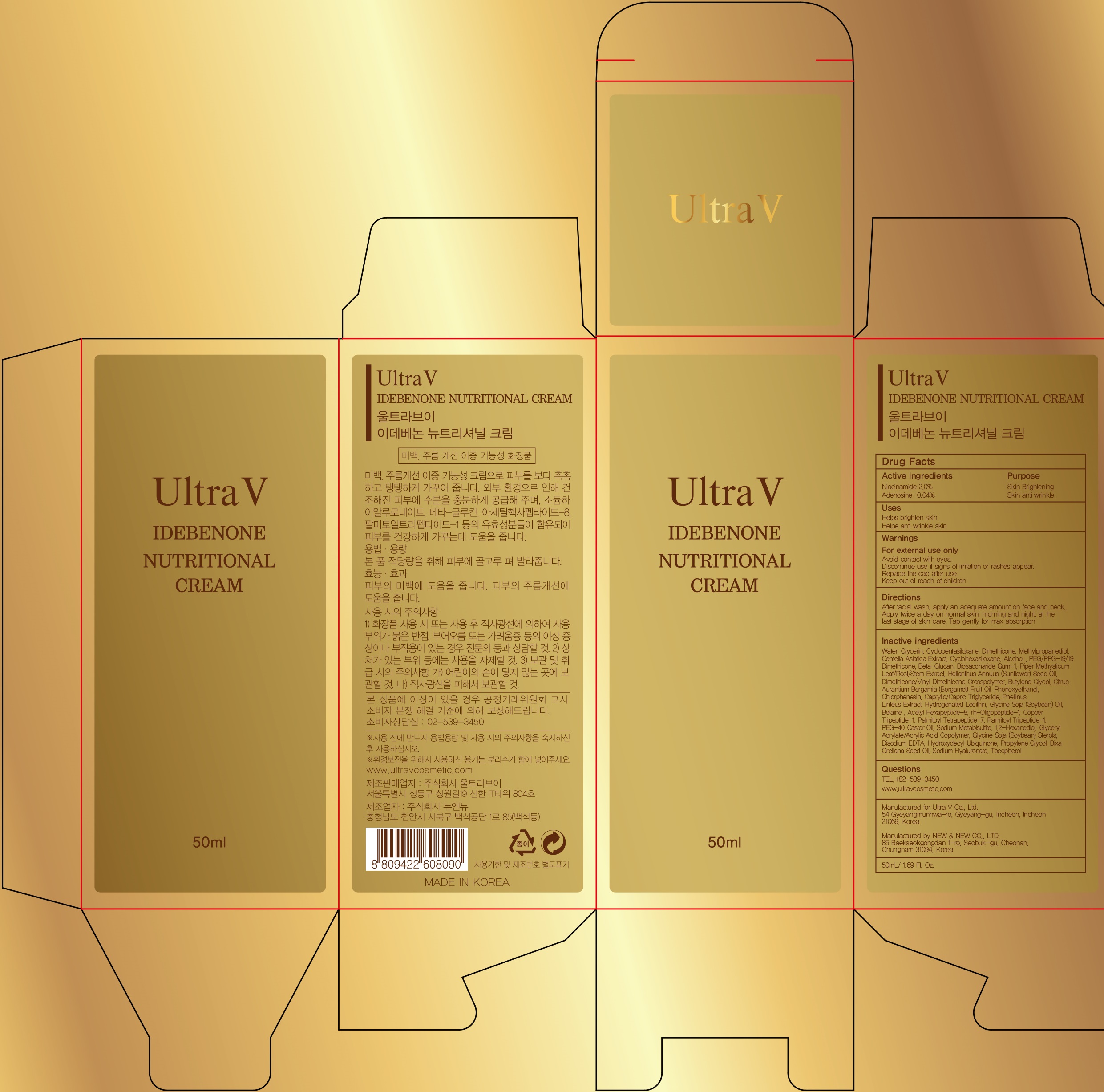 DRUG LABEL: Ultra V IDEBENONE NUTRITIONAL
NDC: 71975-030 | Form: CREAM
Manufacturer: Ultra V Co., Ltd
Category: otc | Type: HUMAN OTC DRUG LABEL
Date: 20200401

ACTIVE INGREDIENTS: Niacinamide 1.0 g/50 mL; Adenosine 0.02 g/50 mL
INACTIVE INGREDIENTS: Water; Glycerin

ACTIVE INGREDIENT

Active ingredients: Niacinamide 2.0%, Adenosine 0.04%

INACTIVE INGREDIENT

Inactive ingredients: Water, Glycerin, Cyclopentasiloxane, Dimethicone, Methylpropanediol, Centella Asiatica Extract, Cyclohexasiloxane, Alcohol , PEG/PPG-19/19 Dimethicone, Beta-Glucan , Biosaccharide Gum-1 , Piper Methysticum Leaf/Root/Stem Extract , Helianthus Annuus (Sunflower) Seed Oil , Dimethicone/Vinyl Dimethicone Crosspolymer , Butylene Glycol , Citrus Aurantium Bergamia (Bergamot) Fruit Oil, Phenoxyethanol, Chlorphenesin, Caprylic/Capric Triglyceride , Phellinus Linteus Extract , Hydrogenated Lecithin , Glycine Soja (Soybean) Oil , Betaine , Acetyl Hexapeptide-8, rh-Oligopeptide-1, Copper Tripeptide-1 , Palmitoyl Tetrapeptide-7, Palmitoyl Tripeptide-1, PEG-40 Castor Oil , Sodium Metabisulfite, 1,2-Hexanediol , Glyceryl Acrylate/Acrylic Acid Copolymer, Glycine Soja (Soybean) Sterols , Disodium EDTA, Hydroxydecyl Ubiquinone , Propylene Glycol, Bixa Orellana Seed Oil , Sodium Hyaluronate, Tocopherol

PURPOSE

Purpose: Skin Brightening, Skin anti wrinkle

WARNINGS

Warnings: For external use only. Avoid contact with eyes. Discontinue use if signs of irritation or rashes appear. Replace the cap after use. Keep out of reach of children.

KEEP OUT OF REACH OF CHILDREN

Uses

Helps brighten skin

Helps anti wrinkle

Directions

Directions: After facial wash, apply an adequate amount on face and neck. Apply twice a day on normal skin, morning and night, at the last stage of skin care. Tap gently for max absorption

QUESTIONS

TEL,+82-539-3450

www.ultravcosmetic.com